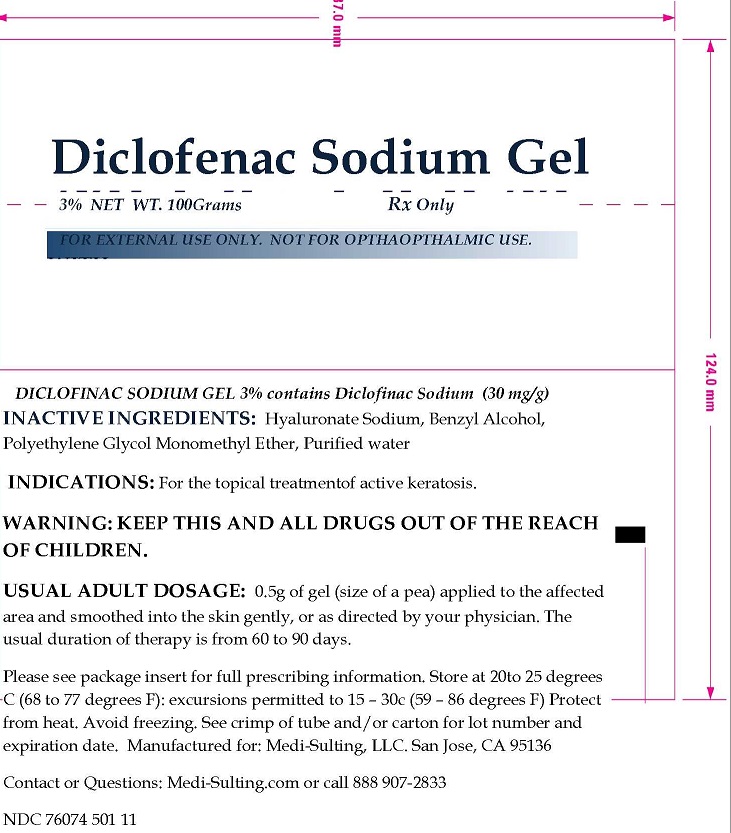 DRUG LABEL: Diclofenac Sodium
NDC: 76074-501 | Form: GEL
Manufacturer: Two Hip Consulting, LLC
Category: prescription | Type: HUMAN PRESCRIPTION DRUG LABEL
Date: 20190206

ACTIVE INGREDIENTS: DICLOFENAC SODIUM 3 g/100 g
INACTIVE INGREDIENTS: HYALURONATE SODIUM; BENZYL ALCOHOL; METHOXY PEG-40; WATER

INDICATIONS: For the topical treatmentof active keratosis.

INACTIVE INGREDIENTS

HYALURONATE SODIU, BENZYL ALCOHOL, POLYETHYLENE GLYCOL MONOMETHYL ETHER, PURIFIED WATER.

USUAL ADULT DOSAGE

0.5G OF GEL (SIZE OF A PEA APPLIED TO AFFECTED AREA AND SMOOTHED INTO SKIN GENTLY, OR AS DIRECTED BY YOUR PHYSICIAN. THE USUAL DURATION OF THERAPY IS FROM 60 TO 90 DAYS.

WARNING

KEEP THIS AND ALL DRUGS OUT OF THE REACH OF CHILDREN.

OTHER SAFETY INFORMATION

Please see package insert for full prescribing information. Store at 20 to 25 degrees C (68 to 77 degrees F): excursions permitted to 15 – 30 C (59 – 86 degrees F) Protect from heat. Avoid freezing. See crimp of tube and/or carton for lot number and expiration date.